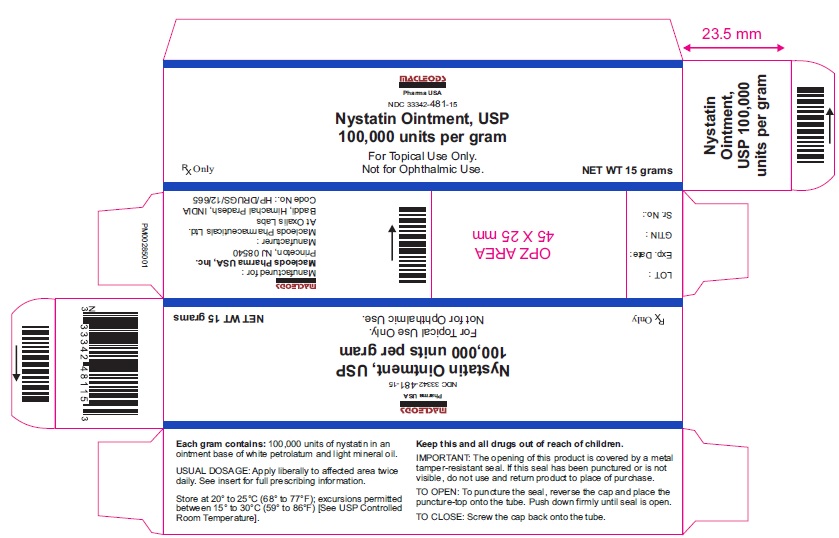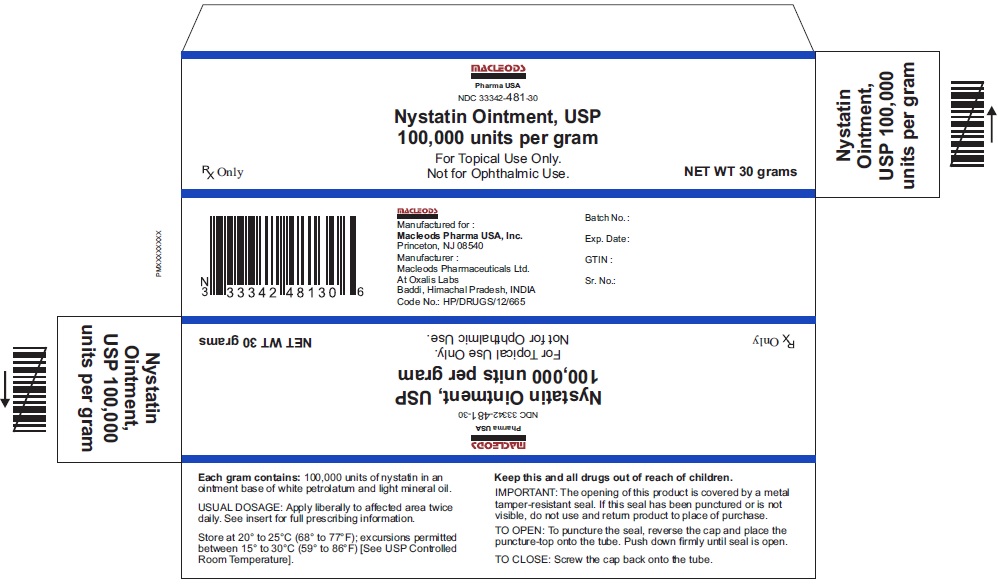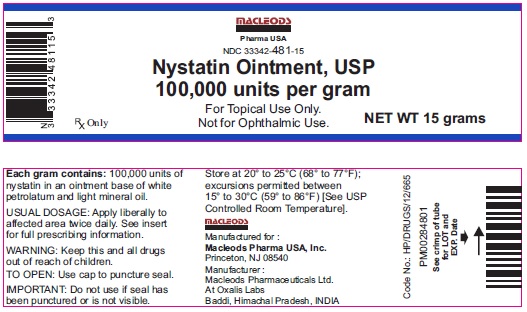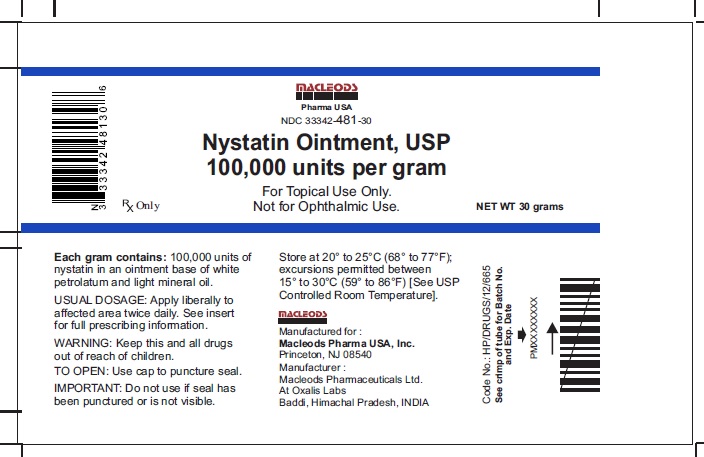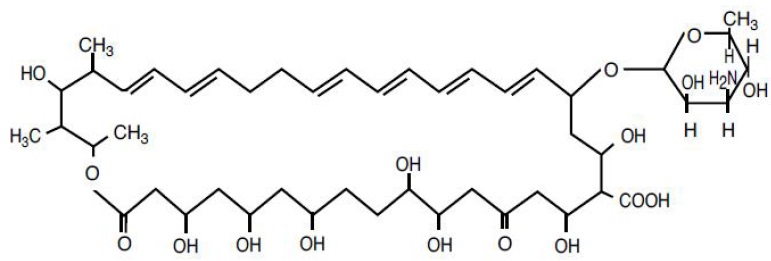 DRUG LABEL: Nystatin
NDC: 33342-481 | Form: OINTMENT
Manufacturer: Macleods Pharmaceuticals Limited
Category: prescription | Type: Human Prescription Drug Label
Date: 20210129

ACTIVE INGREDIENTS: NYSTATIN 100000 1/1 g
INACTIVE INGREDIENTS: LIGHT MINERAL OIL; PETROLATUM

Nystatin Ointment,USP 100,000 units per gram
For Topical Use Only – Not for Ophthalmic Use
Rx only

DESCRIPTION

Nystatin is a polyene antifungal antibiotic drug obtained from Streptomyces nursei
Nystatin Ointment USP, for topical use only, contains 100,000 USP Nystatin Units per gram, in an ointment base of light mineral oil and white petrolatum. The structural formula is as follows:

Molecular Weight 926.13

Molecular Formula C47H75NO17

CLINICAL PHARMACOLOGY

Pharmacokinetics
Nystatin is not absorbed from intact skin or mucous membrane.
Microbiology
Nystatin is an antibiotic which is both fungistatic and fungicidal in vitro against a wide variety of yeasts and yeast-like fungi, including Candida albicans, C. parapsilosis, C. tropicalis, C. guilliermondi, C. pseudotropicalis, C. krusei, Torulopsis glabrata, Tricophyton rubrum, T. mentagrophytes.
Nystatin acts by binding to sterols in the cell membrane of susceptible species resulting in a change in membrane permeability and the subsequent leakage of intracellular components. On repeated subculturing with increasing concentrations of nystatin, Candida albicans does not develop resistance to nystatin.Generally, resistance to nystatin does not develop during therapy. However, other species of 47 75 17 Candida (C. tropicalis, C. guilliermondi, C. krusei, and C. stellatoides) become quite resistant on treatment with nystatin and simultaneously become cross resistant to amphotericin as well. This resistance is lost when the antibiotic is removed.
Nystatin exhibits no appreciable activity against bacteria, protozoa, or viruses.

INDICATIONS AND USAGE

Nystatin Ointment, is indicated in the treatment of cutaneous or mucocutaneous mycotic infections caused by Candida albicans and other susceptible Candida species.
Nystatin Ointment is not indicated for systemic, oral, intravaginal or ophthalmic use.

CONTRAINDICATIONS

Nystatin Ointment is contraindicated in patients with a history of hypersensitivity to any of their components.

PRECAUTIONS

General
Nystatin Ointment should not be used for the treatment of systemic, oral, intravaginal or ophthalmic infections.
If irritation or sensitization develops, treatment should be discontinued and appropriate measures taken as indicated. It is recommended that KOH smears, cultures, or other diagnostic methods be used to confirm the diagnosis of cutaneous or mucocutaneous candidiasis and to rule out infection caused by other pathogens.

INFORMATION FOR THE PATIENTS

Patients using these medications should receive the following information and instructions :
1. The patient should be instructed to use these medications as directed (including the replacement of missed doses). These medications are not for any disorder other than that for which they are prescribed.
2. Even if symptomatic relief occurs within the first few days of treatment, the patient should be advised not to interrupt or discontinue therapy until the prescribed course of treatment is completed.
3. If symptoms of irritation develop, the patient should be advised to notify the physician promptly.

Laboratory Tests

If there is a lack of therapeutic response, KOH smears, cultures, or other diagnostic methods should be repeated.

Carcinogenisis, Mutagenisis, Impairment of Fertility

No long-term animal studies have been performed to evaluate the carcinogenic potential of nystatin. No studies have been performed to determine the mutagenicity of nystatin or its effects on male or female fertility.

Pregnancy: Teratogenic Effects

Animal reproduction studies have not been conducted with any nystatin topical preparation. It also is not known whether these preparations can cause fetal harm when used by a pregnant woman or can affect reproductive capacity. Nystatin topical preparations should be prescribed for a pregnant woman only if the potential benefit to the mother outweighs the potential risk to the fetus.

Nursing Mothers

It is not known whether nystatin is excreted in human milk. Caution should be exercised when nystatin is prescribed for a nursing woman.

Pediatric use

Safety and effectiveness have been established in the pediatric population from birth to 16 years.
See DOSAGE AND ADMINISTRATION

ADVERSE REACTIONS

The frequency of adverse events reported in patients using Nystatin Ointment preparations is less than 0.1%. The more common events that were reported include allergic reactions, burning, itching, rash, eczema, and pain on application.
(See PRECAUTIONS: General.)
To report SUSPECTED ADVERSE REACTIONS, contact Macleods Pharma USA, Inc., at 1-888-943-3210 or 1-855-926-338 or FDA at 1-800-FDA-1088 (www.fda.gov/medwatch).

DOSAGE & ADMINISTRATION

Nystatin Ointment
Adults and Pediatric Patients (Neonates and Older):
Apply liberally to affected areas twice daily or as indicated until healing is complete.

HOW SUPPLIED

Nystatin Ointment (100,000 USP Nystatin Units per gram) is a yellowish ointment available as follows:

NDC 33342-481-15 15 gram tube
NDC 33342-481-30 30 gram tube

Store at 20° to 25°C (68° to 77°F); excursions permitted between 15° to 30°C (59° to 86°F) [See USP Controlled Room Temperature].

Manufactured for:
Macleods Pharma USA, Inc.

Princeton, NJ 08540

Manufacturer:
Macleods Pharmaceuticals Limited
At Oxalis Labs
Baddi, Himachal Pradesh, INDIA

Rev. 01/2021

PACKAGE LABEL.PRINCIPAL DISPLAY PANEL

Nystatin Ointment (100,000 USP Nystatin Units per gram)
Pack Count: 15 g Tube
NDC 33342-481-15
Nystatin Ointment (100,000 USP Nystatin Units per gram)
Pack Count: 15 g Carton
NDC 33342-481-15
Nystatin Ointment (100,000 USP Nystatin Units per gram)
Pack Count: 30 g Tube
NDC 33342-481-30
Nystatin Ointment (100,000 USP Nystatin Units per gram)
Pack Count: 30 g Carton
NDC 33342-481-30